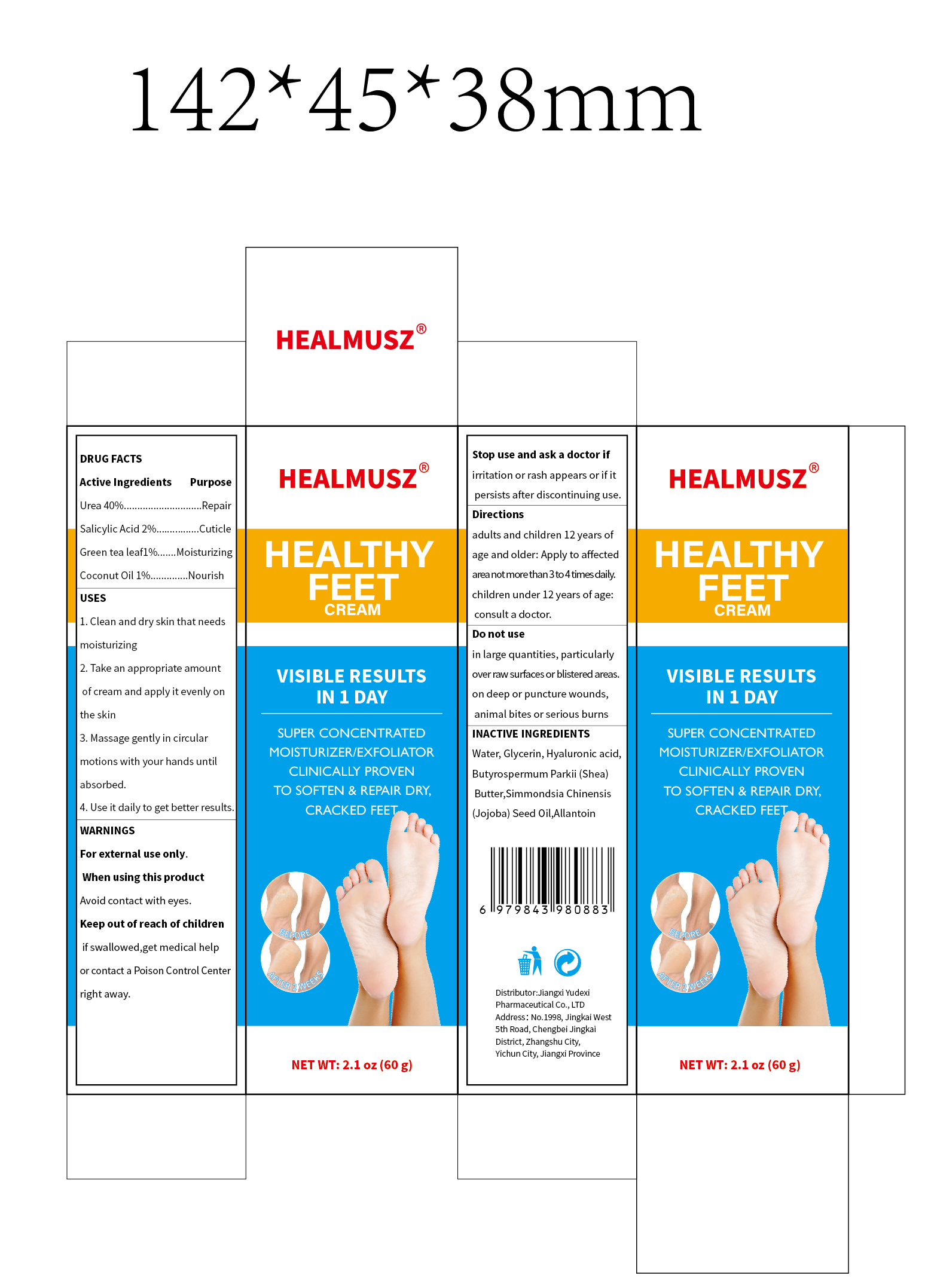 DRUG LABEL: HEALMUSZ  HEALTHY FEET
NDC: 85248-067 | Form: CREAM
Manufacturer: Jiangxi Yudexi Pharmaceutical Co., LTD
Category: otc | Type: HUMAN OTC DRUG LABEL
Date: 20260209

ACTIVE INGREDIENTS: SALICYLIC ACID 2 g/100 g; CAMELLIA SINENSIS LEAF 1 g/100 g; COCONUT OIL 1 g/100 g; UREA 40 g/100 g
INACTIVE INGREDIENTS: SIMMONDSIA CHINENSIS (JOJOBA) SEED OIL; HYALURONIC ACID; BUTYROSPERMUM PARKII (SHEA) BUTTER; GLYCERIN; ALLANTOIN; WATER

85248-067

Active Ingredient

Urea 40% ， Salicylic Acid 2% ， Green tea leafl 1% ， Coconut Oil 1%

Purpose

Repair Cuticle Moisturizing Nourish

Use

1.Clean and dry skin that needs moisturizing
2. Take an appropriate amount of cream and apply it evenly on the skin

3. Massage gently in circular motions with your hands until absorbed.
4. Use it daily to get better results

Warnings

For external use only.

Do not use

in large quantities, particularly over raw surfaces or blistered areas. on deep or puncture wounds, animal bites or serious burns

When Using

Avoid contact with eyes.

Stop Use

irritation or rash appears or if it persists after discontinuing use.

Ask Doctor

irritation or rash appears or if it persists after discontinuing use.

Keep Oot Of Reach Of Children

if swallowed,get medical help or contact a Poison Control Center right away.

Directions

adults and children 12 years of age and older: Apply to affected area not more than 3 to 4times daily children under 12 years of age:consult a doctor.

Inactive ingredients

Water, Glycerin, Hyaluronic acid,Butyrospermum Parkii (Shea)Butter,Simmondsia Chinensis (Jojoba) Seed Oil,Allantoin